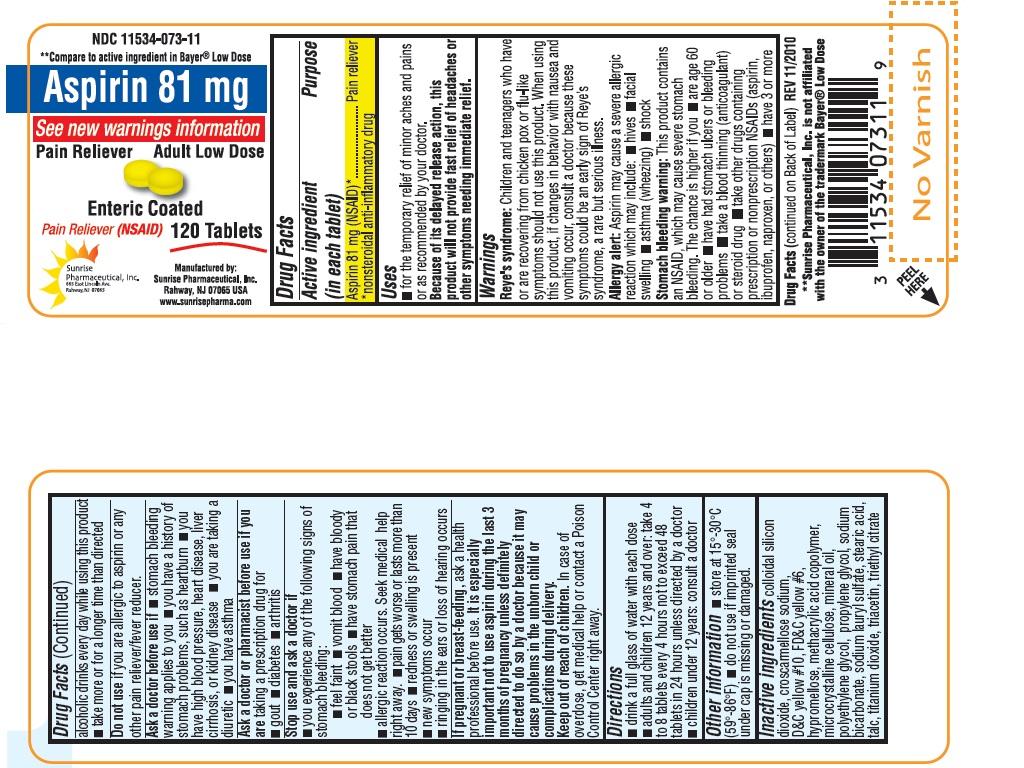 DRUG LABEL: Aspirin
NDC: 11534-073 | Form: TABLET, DELAYED RELEASE
Manufacturer: Sunrise Pharmaceutical Inc
Category: otc | Type: HUMAN OTC DRUG LABEL
Date: 20130801

ACTIVE INGREDIENTS: ASPIRIN 81 mg/1 1
INACTIVE INGREDIENTS: SILICON DIOXIDE; D&C YELLOW NO. 10; FD&C YELLOW NO. 6; HYPROMELLOSE 2208 (100 MPA.S); CELLULOSE, MICROCRYSTALLINE; MINERAL OIL; POLYETHYLENE GLYCOLS; STEARIC ACID; TITANIUM DIOXIDE; TALC; CROSCARMELLOSE SODIUM; PROPYLENE GLYCOL; SODIUM BICARBONATE; SODIUM LAURYL SULFATE; TRIACETIN; TRIETHYL CITRATE; METHACRYLIC ACID - ETHYL ACRYLATE COPOLYMER (1:1) TYPE A 

Unknown Title

OTC - ACTIVE INGREDIENT

Aspirin 81 mg (NSAID)*

*nonsteroidal anti-inflammatory drug

OTC - PURPOSE

Pain reliever

INDICATIONS AND USAGE

- for the temporary relief of minor aches and pains or as recommended by your doctor.

Because of its delayed release action, this product will not provide fast relief of headaches or other symptoms needing immediate relief.

WARNINGS

Reye's Syndrome: Children and teenagers who have or are recovering from chicken pox or flu-like symptoms should not use this product. When using this product, if changes in behavior with nausea and vomiting occur, consult a doctor because these symptoms could be an early sign of Reye's syndrome, a rare but serious illness.

Allergy alert: Aspirin may cause a severe allergic reaction which may include:

- hives
- facial swelling
- asthma (wheezing)
- shock

Stomach bleeding warning: This product contains an NSAID, which may cause severe stomach bleeding. The chance is higher if you

- are age 60 or older
- have had stomach ulcers or bleeding problems
- take a blood thinning (anticoagulant) or steroid drug
- take other drugs containing prescription or nonprescription NSAIDs (aspirin, ibuprofen, naproxen, or others)
- have 3 or more alcoholic drinks everyday while using this product
- take more or for a longer time than directed

OTC - DO NOT USE

If you are allergic to aspirin or any other pain reliever/fever reducer.

OTC - ASK A DOCTOR BEFORE USE IF

- stomach bleeding warning applies to you
- you have a history of stomach problems, such as heartburn
- you have high blood pressure, heart disease, liver cirrhosis, or kidney disease
- you are taking a diuretic
- you have asthma

OTC - ASK A DOCTOR/PHARMACIST BEFORE USE IF YOU ARE

taking a prescription drug for:

- Gout
- Diabetes
- arthritis

OTC - STOP USE AND ASK A DOCTOR IF

- you experience any of the following signs of stomach bleeding:
- feel faint
- vomit blood
- have bloody or black stools
- have stomach pain that does not get better
- allergic reaction occurs. Seek medical help right away.
- pain gets worse or lasts more than 10 days
- redness or swelling is present
- new symptoms occur
- ringing in the ears or loss of hearing occurs

OTC - IF PREGNANT OR BREAST FEEDING

ask a health professional before use. It is especially important not to use aspirin during the last 3 months of pregnancy unless definitely directed to do so by a doctor because it may cause problems in the unborn child or complications during delivery.

OTC - KEEP OUT OF REACH OF CHILDREN

In case of overdose, get medical help or contact a Poison Control Center right away.

DOSAGE AND ADMINISTRATION

- drink a full glass of water with each dose
- adults and children 12 years and over: take 4 to 8 tablets every 4 hours not to exceed 48 tablets in 24 hours unless directed by a doctor
- children under 12 years: consult a doctor

OTHER INFORMATION

- store at 15°-30°C (59°-86°F)
- do not use if seal on the carton is missing or damaged

INACTIVE INGREDIENT

colloidal silicon dioxide, croscarmellose sodium, D&C yellow #10, FD&C yellow #6, hypromellose, methacrylic acid copolymer, microcrystalline cellulose, mineral oil, polyethylene glycol, propylene glycol, sodium bicarbonate, sodium lauryl sulfate, stearic acid, talc, titanium dioxide, triacetin, triethyl citrate.